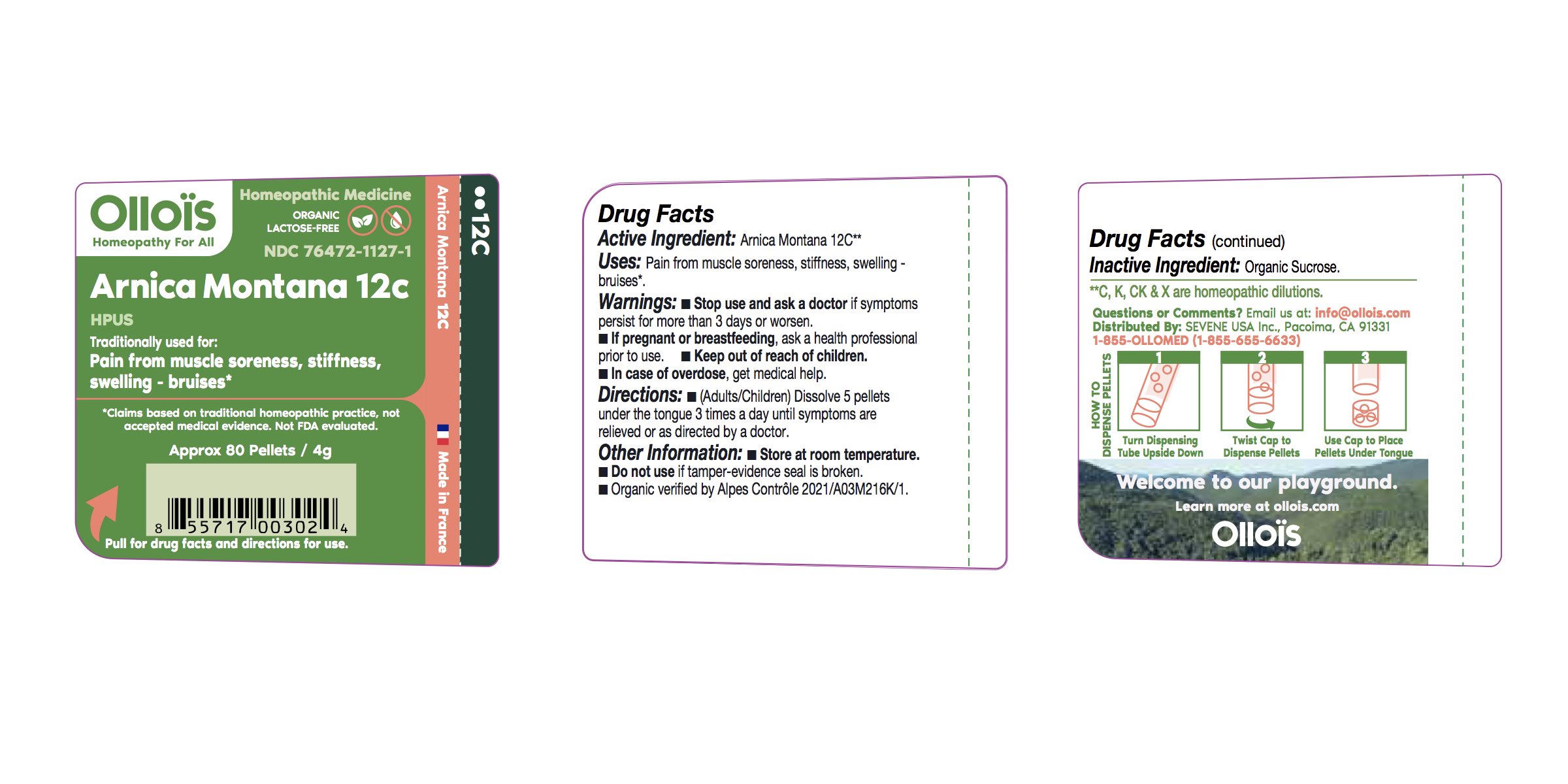 DRUG LABEL: Arnica 12c
NDC: 76472-1127 | Form: PELLET
Manufacturer: SEVENE USA
Category: homeopathic | Type: HUMAN OTC DRUG LABEL
Date: 20250210

ACTIVE INGREDIENTS: ARNICA MONTANA 12 [hp_C]/1 1
INACTIVE INGREDIENTS: SUCROSE

Sevene USA (as PLD) - ARNICA MONTANA 12c (76472-1127)

ACTIVE INGREDIENT

Homeopathic dilution of HPUS Arnica Montana 12c

PURPOSE

Pain from muscle soreness, stiffness, swelling - Bruises*

USE

Condition listed above or as directed by a physician.

WARNINGS

Stop use and ask a physician if symptoms persist for more than 3 days or worsen.

PREGNANCY OR BREAST FEEDING

If pregnant or breast-feeding, ask a health professional before use.

Keep out of reach of children.

Do not use if pellet-dispenser seal is broken.

DIRECTIONS

(adults/children) Dissolve 5 pellets under the tongue 3 times a day until symptoms are relieved or as directed by a physician.

OTHER INFORMATION

Store at room temperature.

INACTIVE INGREDIENT

Sucrose.

QUESTIONS?

www.ollois.com * info@ollois.com* Call 1-855-OLLOMED (Mon-Fri 8am-5pm PST). Made in FRANCE. Not reviewed by the FDA and not guaranteed to be effective. This Homeopathic dilution may not be suseptible to scientific measurement.